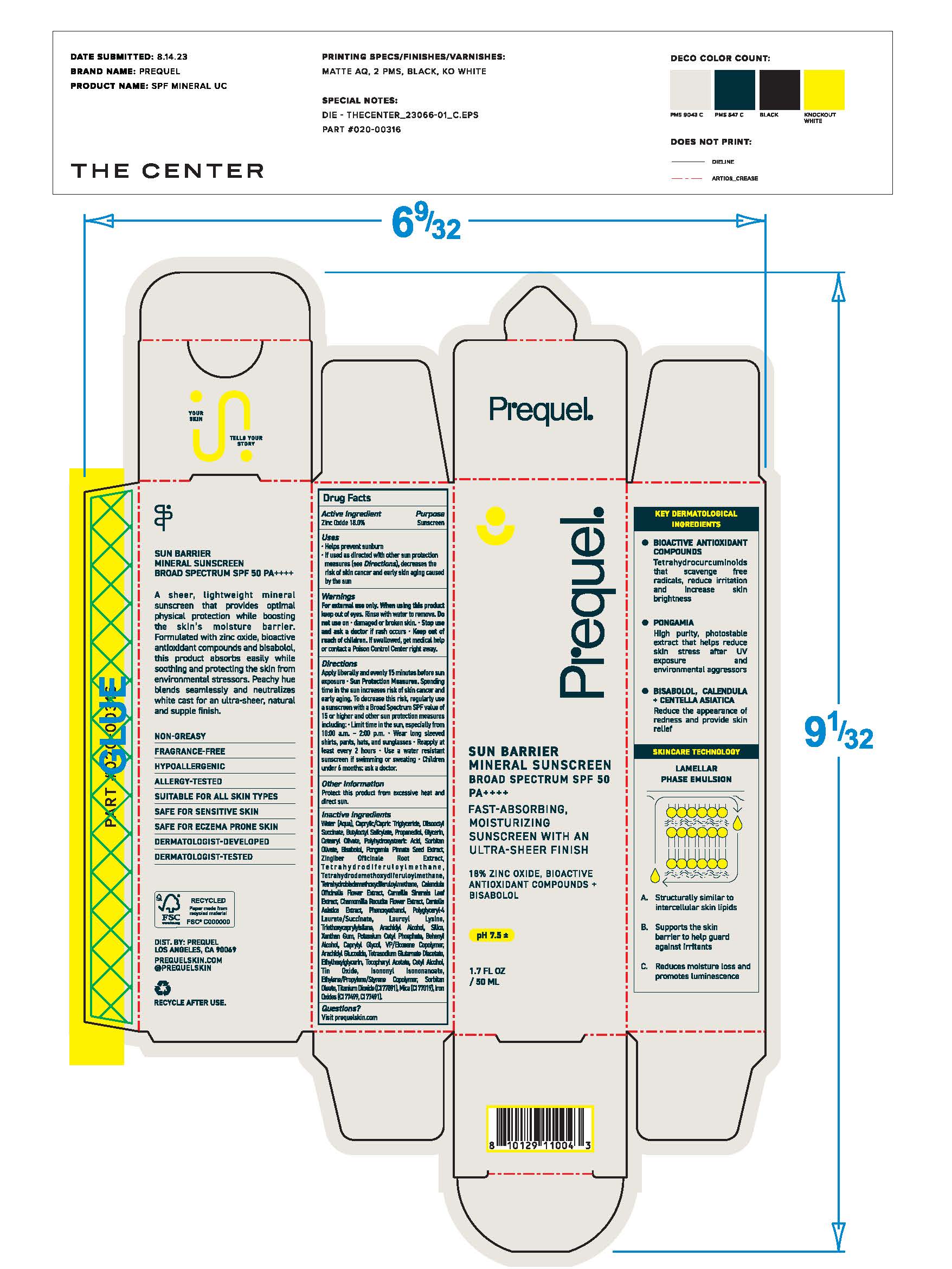 DRUG LABEL: Prequel Sun Barrier Mineral Sunscreen Broad Spectrum SPF 50
NDC: 82800-010 | Form: CREAM
Manufacturer: The Center Brands, LLC
Category: otc | Type: HUMAN OTC DRUG LABEL
Date: 20250117

ACTIVE INGREDIENTS: ZINC OXIDE 18 mg/1 g
INACTIVE INGREDIENTS: WATER; DIISOCETYL ADIPATE; BUTYLOCTYL SALICYLATE; PROPANEDIOL; GLYCERIN; CETEARYL OLIVATE; POLYHYDROXYSTEARIC ACID (2300 MW); SORBITAN OLIVATE; .BETA.-BISABOLOL; PONGAMIA PINNATA SEED; ZINGIBER OFFICINALE WHOLE; TETRAHYDRODIFERULOYLMETHANE; TETRAHYDRODEMETHOXYDIFERULOYLMETHANE; TETRAHYDROBISDEMETHOXYDIFERULOYLMETHANE; CALENDULA OFFICINALIS FLOWER; CAMELLIA SINENSIS SEED; MATRICARIA CHAMOMILLA FLOWERING TOP; CENTELLA ASIATICA; PHENOXYETHANOL; POLYGLYCERYL-4 LAURATE/SUCCINATE; LAUROYL LYSINE; TRIETHOXYCAPRYLYLSILANE; ARACHIDYL ALCOHOL; SILICON; XANTHAN GUM; POTASSIUM CETYL PHOSPHATE; CAPRYLYL GLYCOL; VINYLPYRROLIDONE/EICOSENE COPOLYMER; ARACHIDYL GLUCOSIDE; TETRASODIUM GLUTAMATE DIACETATE; ETHYLHEXYLGLYCERIN; CETYL ALCOHOL; STANNIC OXIDE; ISONONYL ISONONANOATE; SORBITAN MONOOLEATE; TITANIUM DIOXIDE; MICA; BROWN IRON OXIDE

DRUG FACTS

Active Ingredients

Zinc Oxide 18%

Uses

• helps prevent sunburn • if used as directed with other
sun protection measures (see Directions), decreases the
risk of skin cancer and early skin aging caused by the sun

Warnings

For external use only
Do not use on damaged or broken skin.
When using this product keep out of eyes. Rinse with water to remove.
Stop use and ask a docor if rash occurs
Keep out of reach of children. If swalled, get medical help or contact a Poison Control Center right away.

Directions

• apply generously 15 minutes before sun exposure
• reapply: •at least every 2 hours.

• use a water resistant sunscreen if swimming or sweating
• Sun Protection Measures. Spending time in the sun

increases your risk of skin cancer and early skin aging. To decrease
this risk, regularly use a sunscreen with a Broad Spectrum SPF
value of 15 or higher and other sun protection measures including:
• limit time in the sun, especially from 10 a.m. - 2 p.m.
• wear long-sleeved shirts, pants, hats, and sunglasses
• children under 6 months of age: Ask a doctor

Inactive ingredients

Water (Aqua), Caprylic/Capric Triglyceride, Diisooctyl Succinate, Butyloctyl Salicylate, Propanediol, Glycerin, Cetearyl Olivate, Polyhydroxystearic Acid, Sorbitan Olivate, Polyhydroxystearic Acid, Sorbitan Olivate, Bisabolol, Pongamia Pinnata Seed Extract, Zingiber Officinale Root Extract, Tetrahydrodiferuloylmethane, Tetrahydrodemethoxydiferuloylmethane, Tetrahydrodemethoxydiferuloylmethane, Calendula Officinalis Flower Extract, Camellia Sinensis Leaf Extract, Chamomilla Recutita Flower Extract, Centella Asiatica Extract, Phenoxyethanol, Polyglyceryl-4 Laurate/Succinate, Lauroyl Lysine, Triethoxycaprylylsilane, Arachidyl Alcohol, Silica, Xanthan Gum, Potassium Cetyl Phosphate, Behenyl Alcohol, Caprylyl Glycol, VP/Eicosene Copolymer, Arachidyl Glucoside, Tetrasodium Glutamate Diacetate, Ethylhexylglycerin, Tocopheryl Acetate, Cetyl Alcohol, Tin Oxide, Isononyl Isononanoate, Ethylene/Propylene/Styrene Copolymer, Soribitan Oleate, Titanium Dioxide (CI 77891), Mica (CI 77019), Iron Oxides (CI 77499, CI 77491)

Other Information

• protect the product in this container from excessive
heat and direct sun

Questions?

Visit prequelskin.com

Keep out of reach of children

Prupose

Sunscreen